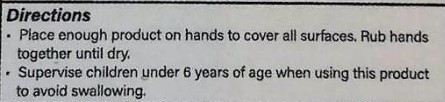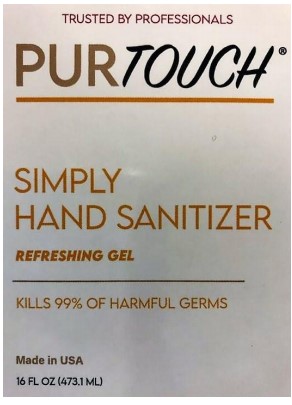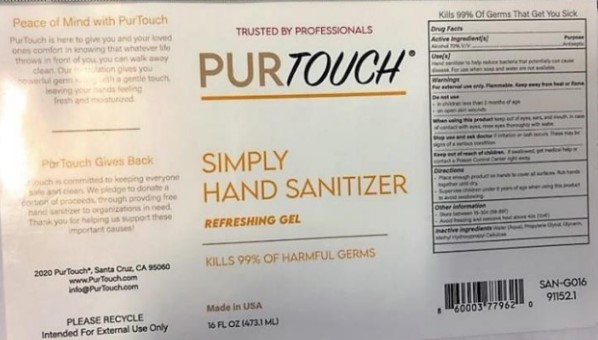 DRUG LABEL: Howe, Consulting
NDC: 73333-016 | Form: LIQUID
Manufacturer: Nutrix International, LLC.
Category: otc | Type: HUMAN OTC DRUG LABEL
Date: 20200507

ACTIVE INGREDIENTS: ALCOHOL 0.74 g/473 g
INACTIVE INGREDIENTS: HYPROMELLOSES 0.007 g/473 g; WATER 0.235 g/473 g; GLYCERIN 0.008 g/473 g; PROPYLENE GLYCOL 0.01 g/473 g

ACTIVE INGREDIENT(S)

Alcohol 70% v/v.

PURPOSE

Antiseptic

Use[s]

Hand Sanitizer to help reduce bacteria that potentially can cause disease. For use when soap and water are not available.

Warnings

For external use only. Flammable. Keep away from heat or flame.

Do not use

- On children less than 2 months of age.
- On open skin wounds.

When using

When using this product keep out of eyes, ears, mouth. In case of contact with eyes, rinse thoroughly with water.

Stop use

Stop use and ask doctor if irritation or rash occurs. These may be signs of a serious condition.

Keep out of reach of children

If swallowed, get medical help or contact a Poison Control Center right away.

Directions

Place enough product on hands to cover all surfaces.
Rub hands together until dry.
Supervise children under age of 6 when using this product to avoid swallowing.

Other Information

- Store between 15-30°C (59-86°F)
- Avoid freezing and excessive heat above 40°C (104°F)

Inactive Ingredients

Water (Aqua), Propylene Glycol, Glycerin, Methyl hydroxypropyl Cellulose

Drug Facts Panel

Label